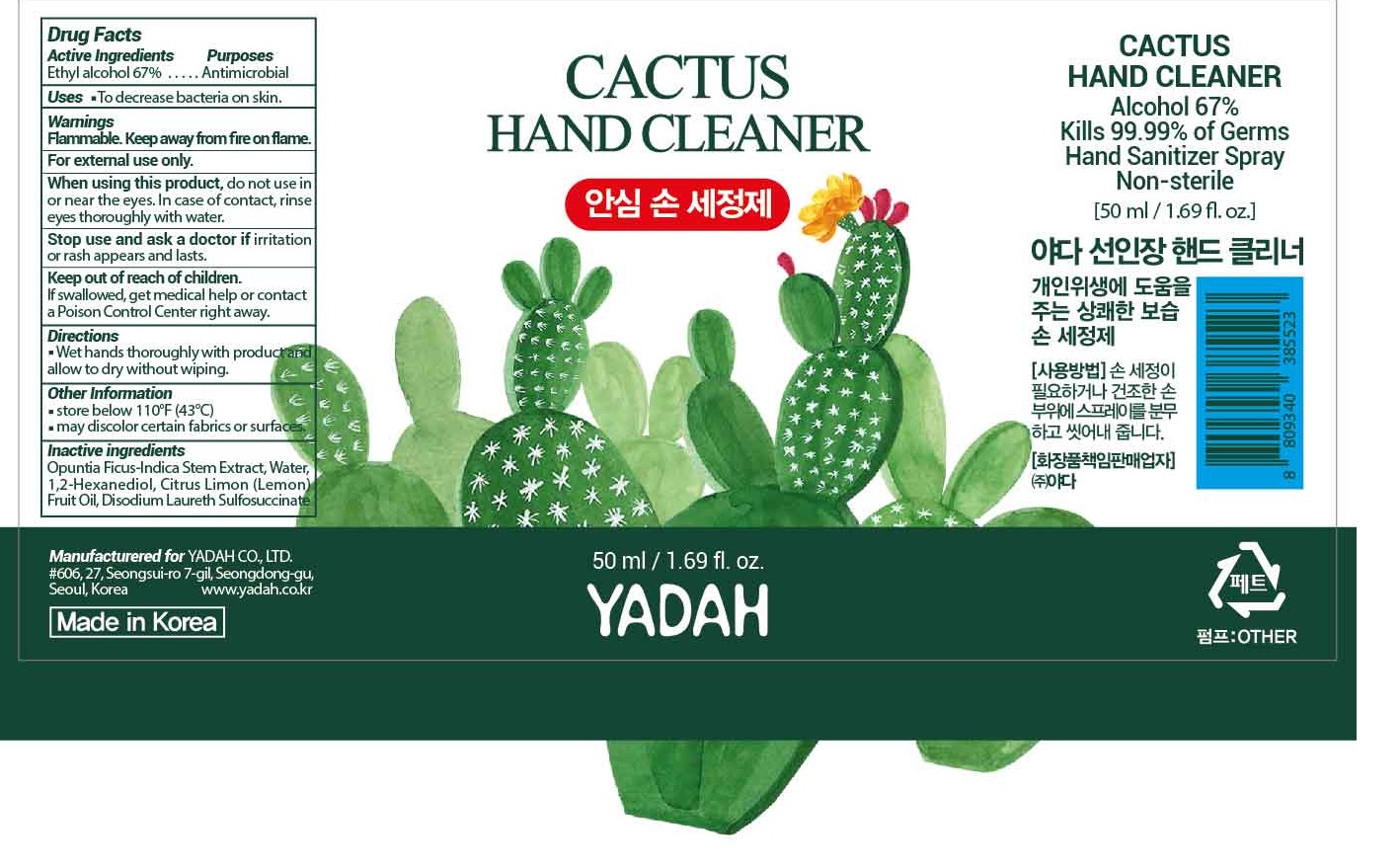 DRUG LABEL: CACTUS HAND CLEANER
NDC: 71026-010 | Form: SPRAY
Manufacturer: YADAH Co., Ltd.
Category: otc | Type: HUMAN OTC DRUG LABEL
Date: 20200410

ACTIVE INGREDIENTS: ALCOHOL 0.67 g/1 mL
INACTIVE INGREDIENTS: OPUNTIA FICUS-INDICA STEM; WATER; 1,2-HEXANEDIOL; CITRUS X LIMON FRUIT OIL; DISODIUM LAURETH SULFOSUCCINATE

71026-010_CACTUS HAND CLEANER

Active ingredient

Ethyl alcohol 67%

Purpose

Antimicrobial

Use

- To decrease bacteria on skin

Warnings

Flammable. Keep away from fire or flame.

For external use only

When using this product do not use in or near the eyes. In case of contact, rinse eyes thoroughly with water.

Stop use and ask a doctor if irritation or rash appears and lasts

Keep out of reach of children.

Other information

- Store below 110°F (43°C)
- May discolor certain fabrics or surfaces

Directions

Wet hands thoroughly with product and allow to dry without wiping

Inactive ingredients

Opuntia Ficus-Indica Stem Extract, Water, 1,2-Hexanediol, Citrus Limon (Lemon) Fruit Oil, Disodium Laureth Sulfosuccinate